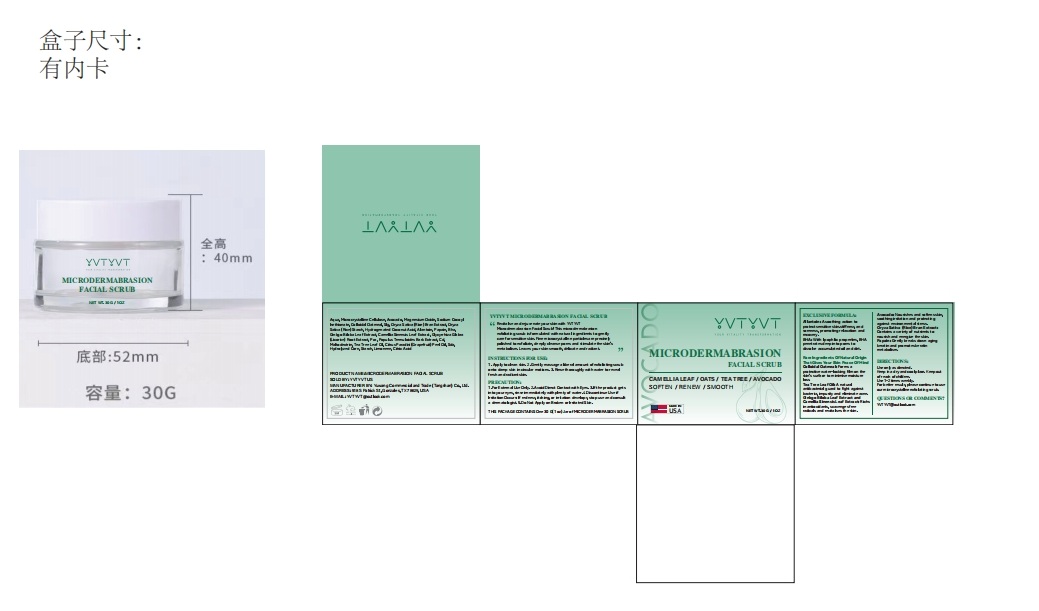 DRUG LABEL: YVTYVT MICRODERMABRASION FACIAL SCRUB
NDC: 85212-0018 | Form: OINTMENT
Manufacturer: Beijing JUNGE Technology Co., Ltd.
Category: otc | Type: HUMAN OTC DRUG LABEL
Date: 20250228

ACTIVE INGREDIENTS: MICROCRYSTALLINE CELLULOSE 3 g/100 g; BUTYROSPERMUM PARKII (SHEA) BUTTER 3 g/100 g; BEESWAX 1 g/100 g; BETAINE 2 g/100 g
INACTIVE INGREDIENTS: PROPYLENE GLYCOL 5 g/100 g; PEG-100 STEARATE 1 g/100 g; TOCOPHEROL 0.5 g/100 g; XANTHAN GUM 0.1 g/100 g; SIMMONDSIA CHINENSIS (JOJOBA) SEED OIL 2 g/100 g; STEARIC ACID 1 g/100 g; LACTIC ACID 2 g/100 g; CAMELLIA SINENSIS LEAF 0.5 g/100 g; GLYCERYL CAPRYLATE 0.1 g/100 g; ETHYLHEXYL PALMITATE 2 g/100 g; ALLANTOIN 0.1 g/100 g; BEHENYL ALCOHOL 0.5 g/100 g; CARBOMER 0.1 g/100 g; 1,2-HEXANEDIOL 0.1 g/100 g; CHRYSANTHELLUM INDICUM WHOLE 0.2 g/100 g; GLYCERYL STEARATE 1 g/100 g; ALOE BARBADENSIS LEAF 0.2 g/100 g; HYDROXYPROPYL METHYLCELLULOSE 0.2 g/100 g; CLADOSIPHON OKAMURANUS WHOLE 0.1 g/100 g; PEG-20 METHYL GLUCOSE SESQUISTEARATE 1 g/100 g; BUTYLENE GLYCOL 5 g/100 g; AQUA 65.3 g/100 g; CETEARYL ALCOHOL 3 g/100 g

DOSAGE AND ADMINISTRATION

NET WT. 30 G /1 OZ

INDICATIONS AND USAGE

1. Apply to clean skin.

2. Gently massage a liberal amount of exfoliating scrub onto damp skin in circular motions.

3. Rinse thoroughly with water to reveal fresh and radiant skin.

PRECAUTIONS

1.For External Use Only.

2.Avoid Direct Contact with Eyes.

3.If the product gets into your eyes, rinse immediately with plenty of water.

4.Discontinue Use if Irritation Occurs: If redness, itching, or irritation develops, stop use and consult a dermatologist.

5.Do Not Apply on Broken or Irritated Skin.

INACTIVE INGREDIENT

AQUA
BUTYLENE GLYCOL
PROPYLENE GLYCOL
CETEARYL ALCOHOL
ETHYLHEXYL PALMITATE
LACTIC ACID
SIMMONDSIA CHINENSIS (JOJOBA) SEED OIL
STEARIC ACID
PEG-100 STEARATE
GLYCERYL STEARATE
PEG-20 METHYL GLUCOSE SESQUISTEARATE
BEHENYL ALCOHOL
TOCOPHEROL
CAMELLIA SINENSIS LEAF EXTRACT
CHRYSANTHELLUM INDICUM EXTRACT
ALOE BARBADENSIS LEAF EXTRACT
HYDROXYPROPYL METHYLCELLULOSE
CLADOSIPHON OKAMURANUS EXTRACT
CARBOMER
XANTHAN GUM
1,2-HEXANEDIOL
ALLANTOIN
GLYCERYL CAPRYLATE

PURPOSE

Exfoliate, deeply cleanse pores and stimulate the skin's metabolism.

Keep out of reach of children. If swallowed, get medical help or contact a Poison Control Center right away.

WARNINGS

For external use only. Keep out of reach of children.Avoid contact with eyes.